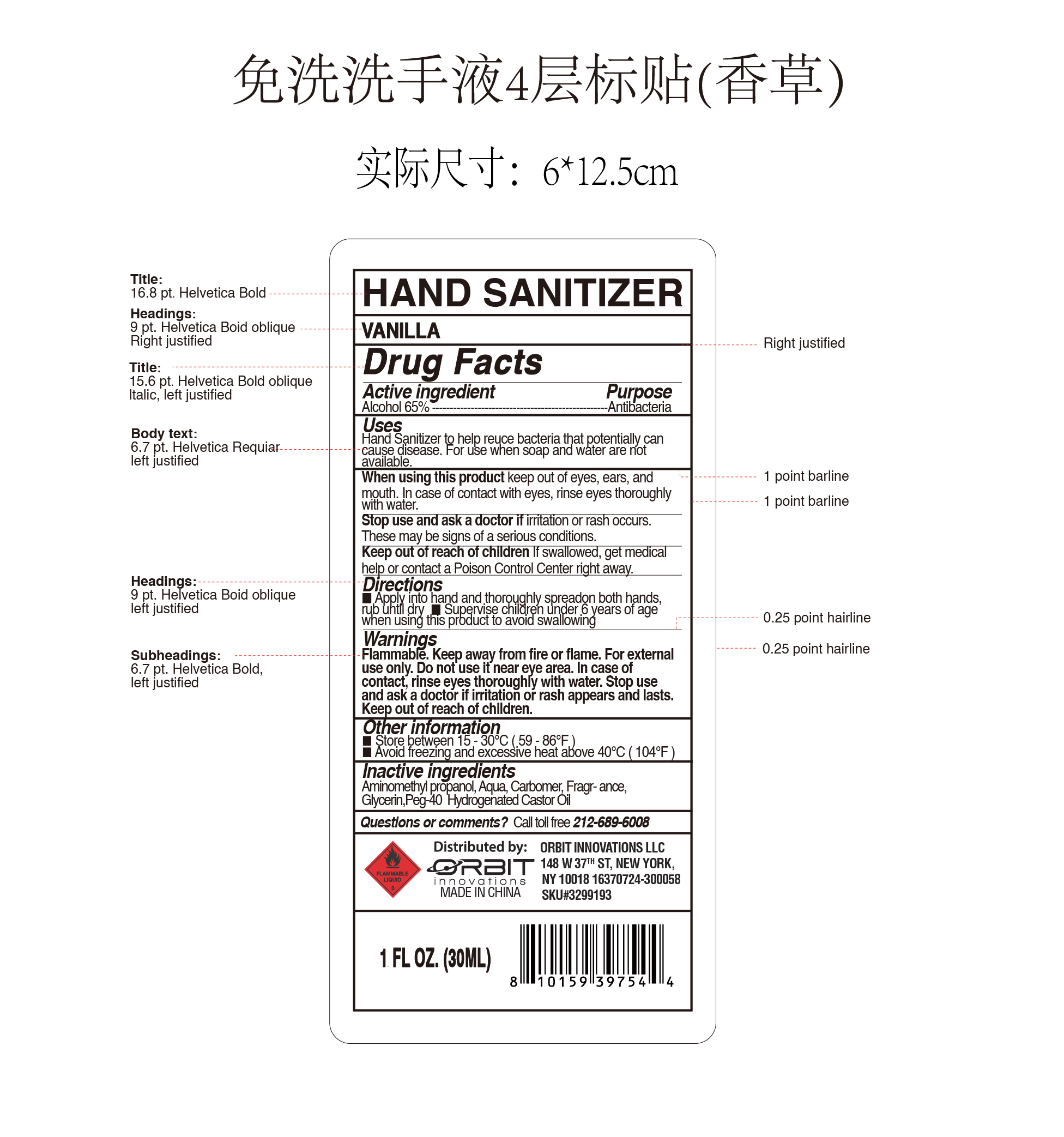 DRUG LABEL: ORBIT INNOVATIONS HAND SANITIZER COTTON VANILLIA
NDC: 73928-061 | Form: GEL
Manufacturer: Kingkey MBC Life Technology Group Co.,Ltd
Category: otc | Type: HUMAN OTC DRUG LABEL
Date: 20250205

ACTIVE INGREDIENTS: ALCOHOL 65 mL/100 mL
INACTIVE INGREDIENTS: AMINOMETHYLPROPANOL; CARBOMER 980; GLYCERIN; WATER; PEG-40 HYDROGENATED CASTOR OIL

ORBIT INNOVATIONS HAND SANITIZER （VANILLIA)

Active ingredient

Alcohol 65% ------------------------------- Antibacterial

Users

Effective in eliminating harmful germs and bacteria when soap and water are unavailable.

Purpose

Uses

Hand Sanitizer to help reduce bacteria that potentially can cause disease. For use when soap and water are not available

Warnings

Flammable.

Keep away from fire or flames.

For external use only.

Do not use it near eye area.

In case of contact, rinse eyes throughly with water.

Stop use and ask a doctor if irritation or rash appears and lasts.

Keep out of reach of children.

Keep out of reach of children.

If swallowed, get medical help or contact a Poison Control Center right away.

Directions

- Place enough product in palm to thoroughly cover hands.Rub hands together briskly until dry.
- Supervise children under 6 years of age when using this product to avoid swallowing.

Inactives ingredient

Aminomethylpropanol,Aqua,Carbomer, Fragrance,Glycerin,Peg-40 Hydrogenated castor oil

Other information

Store between 15 - 30c (59 - 86f)

Avoid freezing and excessive heat above 40c (104F)

Questions or comments？

call toll free 212-68906008